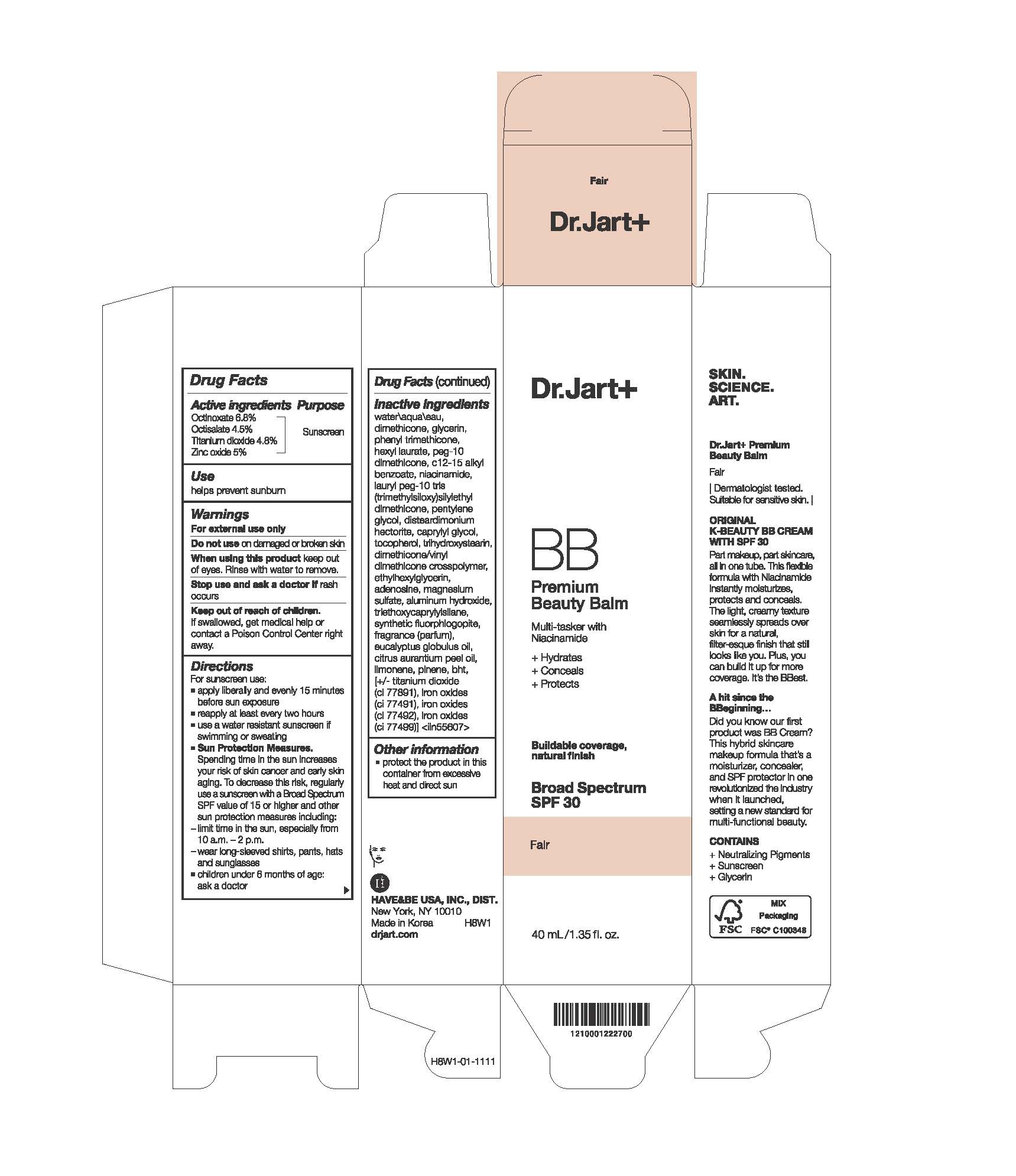 DRUG LABEL: PREMIUM BEAUTY BALM BROAD SPECTRUM SPF 30
NDC: 49404-157 | Form: LOTION
Manufacturer: Have & Be Co., Ltd.
Category: otc | Type: HUMAN OTC DRUG LABEL
Date: 20260210

ACTIVE INGREDIENTS: OCTISALATE 45 mg/1 mL; OCTINOXATE 68 mg/1 mL; ZINC OXIDE 50 mg/1 mL; TITANIUM DIOXIDE 48 mg/1 mL
INACTIVE INGREDIENTS: HEXYL LAURATE; C12-15 ALKYL BENZOATE; ETHYLHEXYLGLYCERIN; TRIETHOXYCAPRYLYLSILANE; LIMONENE, (+)-; CI 77491; BHT; DIMETHICONE; GLYCERIN; WATER; PEG-10 DIMETHICONE (600 CST); ADENOSINE; MAGNESIUM POTASSIUM ALUMINOSILICATE FLUORIDE; CI 77492; NIACINAMIDE; TRIHYDROXYSTEARIN; PHENYL TRIMETHICONE; TOCOPHEROL; CITRUS AURANTIUM PEEL OIL; CAPRYLYL GLYCOL; DIMETHICONE/VINYL DIMETHICONE CROSSPOLYMER (HARD PARTICLE); MAGNESIUM SULFATE; ALUMINUM HYDROXIDE; EUCALYPTUS GLOBULUS OIL; CI 77499; PENTYLENE GLYCOL; DISTEARDIMONIUM HECTORITE; PINENE

PREMIUM BEAUTY BALM BROAD SPECTRUM SPF 30

Active ingredients

OCTINOXATE 6.8%
OCTISALATE 4.5%
TITANIUM DIOXIDE 4.8%
ZINC OXIDE 5%

Purpose

Sunscreen

Use

helps prevent sunburn

Warnings

For external use only

Do not use

on damaged or broken skin

When using this product

keep out of eyes. Rinse with water to remove.

Stop use and ask a doctor if

rash occurs

Keep out of reach of children.

If swallowed, get medical help or contact a Poison Control Center right away.

Directions

For sunscreen use:
apply liberally and evenly 15 minutes before sun exposure
reapply at least every two hours
use a water resistant sunscreen if swimming or sweating
Sun Protection Measures. Spending time in the sun increases your risk of skin cancer and early skin aging. To decrease this risk, regularly use a sunscreen with a Broad Spectrum SPF value of 15 or higher and other sun protection measures including:

limit time in the sun, especially from 10 a.m.–2 p.m.
wear long-sleeved shirts, pants, hats and sunglasses

children under 6 months of age: ask a doctor

Inactive Ingredients

water\aqua\eau , dimethicone , glycerin , phenyl trimethicone , hexyl laurate , peg-10 dimethicone , c12-15 alkyl benzoate , niacinamide , lauryl peg-10 tris(trimethylsiloxy)silylethyl dimethicone , pentylene glycol , disteardimonium hectorite , caprylyl glycol , tocopherol , trihydroxystearin , dimethicone/vinyl dimethicone crosspolymer , ethylhexylglycerin , adenosine , magnesium sulfate , aluminum hydroxide , triethoxycaprylylsilane , synthetic fluorphlogopite , fragrance (parfum) , eucalyptus globulus oil , citrus aurantium peel oil , limonene , pinene , bht , [+/- titanium dioxide (ci 77891) , iron oxides (ci 77491) , iron oxides (ci 77492) , iron oxides (ci 77499)] <iln55607>

Other information

protect the product in this container from excessive heat and direct sun

PACKAGE LABEL

RB Premium
Beauty Balm
Multi-tasker with
Niacinamide
+ Hydrates
+ Conceals
+ Protects

Buildable coverage,
natural finish
Broad Spectrum

SPF 30

40 ml/1 .35 fl. oz.